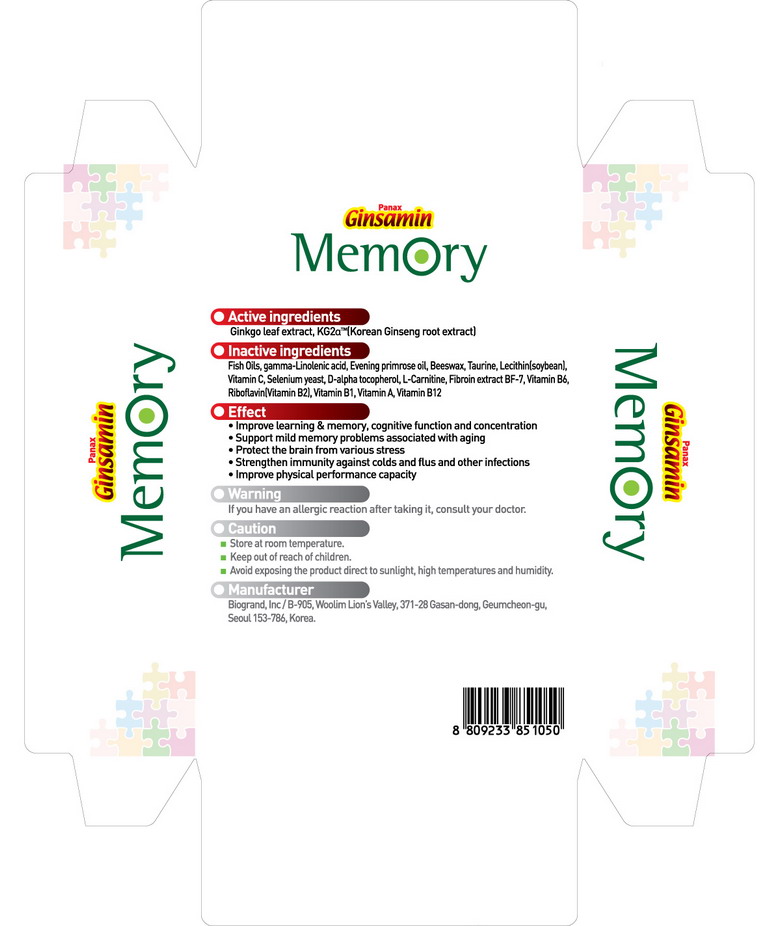 DRUG LABEL: Ginsamin Memory
NDC: 44738-4001 | Form: CAPSULE
Manufacturer: BioGrand Co., Ltd
Category: otc | Type: HUMAN OTC DRUG LABEL
Date: 20100306

ACTIVE INGREDIENTS: GINKGO 100.2 mg/1 1; ASIAN GINSENG 75 mg/1 1

Drug Facts

Active Ingredient: Ginkgo leaf extract, Ginseng root extract

DESCRIPTION

Product name
Ginsamin Memory
Active ingredients
Ginkgo leaf extract, Korean ginseng root extract
Inactive ingredients
fish oil, gamma-linolenic acid, evening promise oil, beeswax, taurine, lecithin,
vitamin C, selenium yeast, D-alpha tocopherol, L-carnitine, vitamin B6,
riboflavin, vitamin B1, vitamin A, vitamin B12
Effect
• improve learning and memory, cognitive function and concentration
• support mild memory problems associated with aging
• protect the brain from various stress
• strengthen immunity against colds and flus and other infections
• improve physical performance capacity
Warning
If you have an allergic reaction after taking it, consult your doctor
Caution
• Store at room temperature.
• Keep out of reach of children.
• Avoid exposing the product direct to sunlight, high temperatures and humidity.
• Manufacturer
Manufacturer
Biogrand, lnc / B-905, Woolim Lion’s Valley, 371-28 Gasan-dong, Geumcheon-gu, Seoul 153-786, Korea